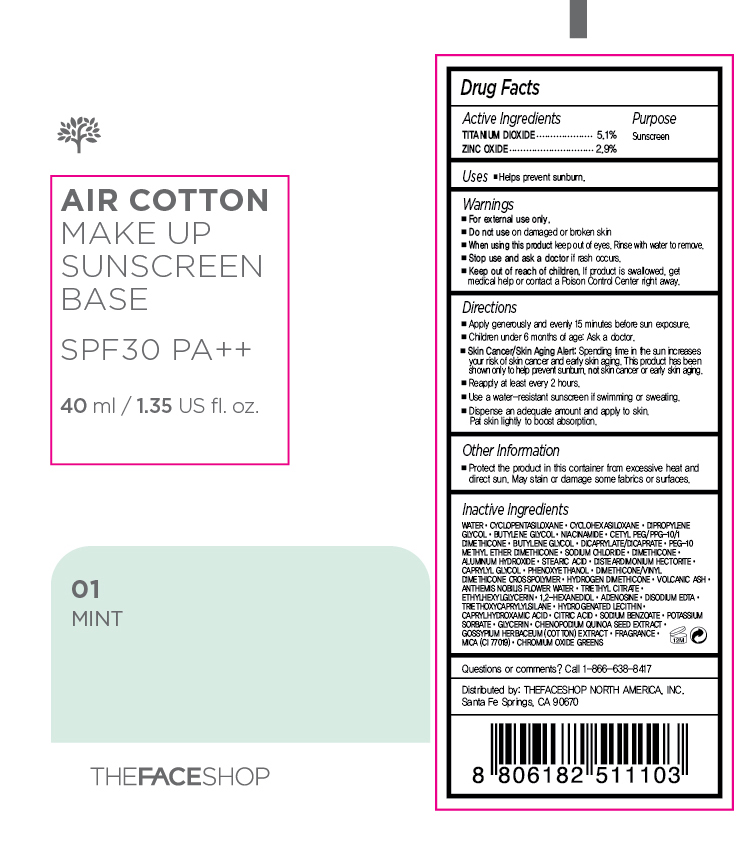 DRUG LABEL: AIR COTTON
NDC: 51523-362 | Form: CREAM
Manufacturer: THEFACESHOP CO., LTD.
Category: otc | Type: HUMAN OTC DRUG LABEL
Date: 20151001

ACTIVE INGREDIENTS: TITANIUM DIOXIDE 2.04 g/40 mL; ZINC OXIDE 1.16 g/40 mL
INACTIVE INGREDIENTS: WATER

TFS AIR COTTON MAKE UP BASE SPF30 PA++ 01 MINT 34200362

Active Ingredients

Titanium Dioxide 5.1 %
Zinc Oxide 2.9 %

Purpose

Sunscreen
Sunscreen

Uses:

Helps prevent sunburn.

Warnings:

For external use only.

Do not use on damaged or broken skin

When using this product keep out of eyes. Rinse with water to remove.

Stop use and ask a doctor if rash occurs.

Keep out of reach of children. If product is swallowed, get medical help or contact a Poison Control Center right away.

Directions

Apply generously and evenly 15 minutes before sun exposure.
Children under 6 months of age: Ask a doctor.
Skin Cancer/Skin Aging Alert: Spending time in the sun increases your risk of skin cancer and early skin aging. This product has been shown only to help prevent sunburn, not skin cancer or early skin aging.
Reapply at least every 2 hours.
Use a water-resistant sunscreen if swimming or sweating.

Dispense an adequate amount and apply to skin. Pat skin lightly to boost absorption.

OTHER SAFETY INFORMATION

Protect the product in this container from excessive heat and direct sun.

May stain or damage some fabrics or surfaces.

Inactive Ingredients:

Water, Cyclopentasiloxane, Cyclohexasiloxane, Dipropylene Glycol, Butylene Glycol, Niacinamide, Cetyl PEG/PPG-10/1 Dimethicone, Butylene Glycol, Dicaprylate/Dicaprate, PEG-10 Methyl Ether Dimethicone, Sodium Chloride, Dimethicone, Aluminum Hydroxide, Stearic Acid, Disteardimonium Hectorite, Caprylyl Glycol, Phenoxyethanol, Dimethicone/Vinyl Dimethicone Crosspolymer, Hydrogen Dimethicone, Volcanic Ash, Anthemis Nobilis Flower Water, Triethyl Citrate, Ethylhexylglycerin, 1,2-Hexanediol, Adenosine, Disodium EDTA, Triethoxycaprylylsilane, Hydrogenated Lecithin, Caprylhydroxamic Acid, Citric Acid, Sodium Benzoate, Potassium sorbate, Glycerin, Chenopodium Quinoa Seed Extract, Gossypium Herbaceum (Cotton) Extract, Fragrance, Mica (CI 77019), Chromium Oxide Greens

Questions or comments? Call 1-866-638-8417

Distributed by:

THEFACESHOP NORTH AMERICA, INC.

Santa Fe Springs, CA 90670

PACKAGE LABEL

AIR COTTON

MAKE UP SUNSCREEN BASE

SPF 30 PA ++

01 MINT